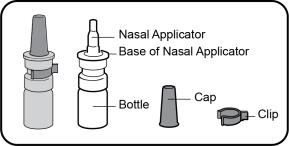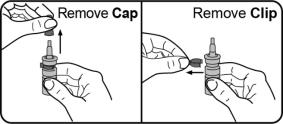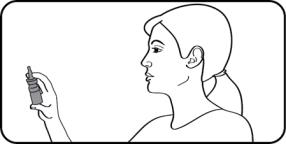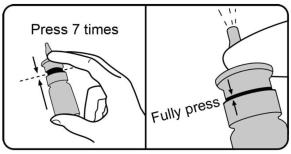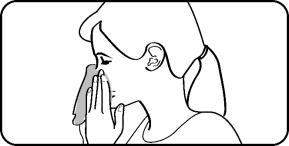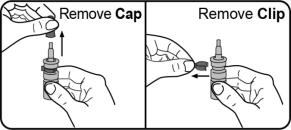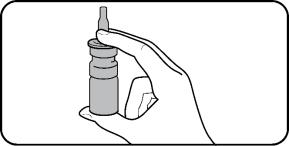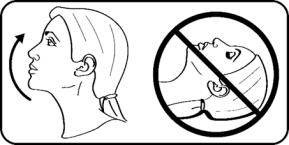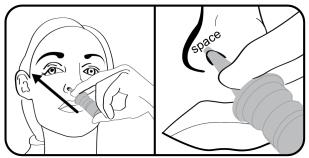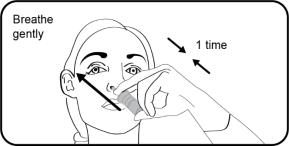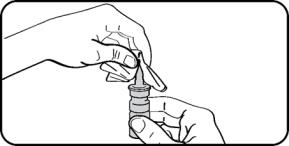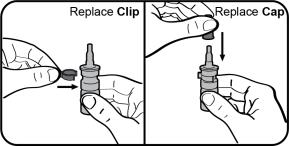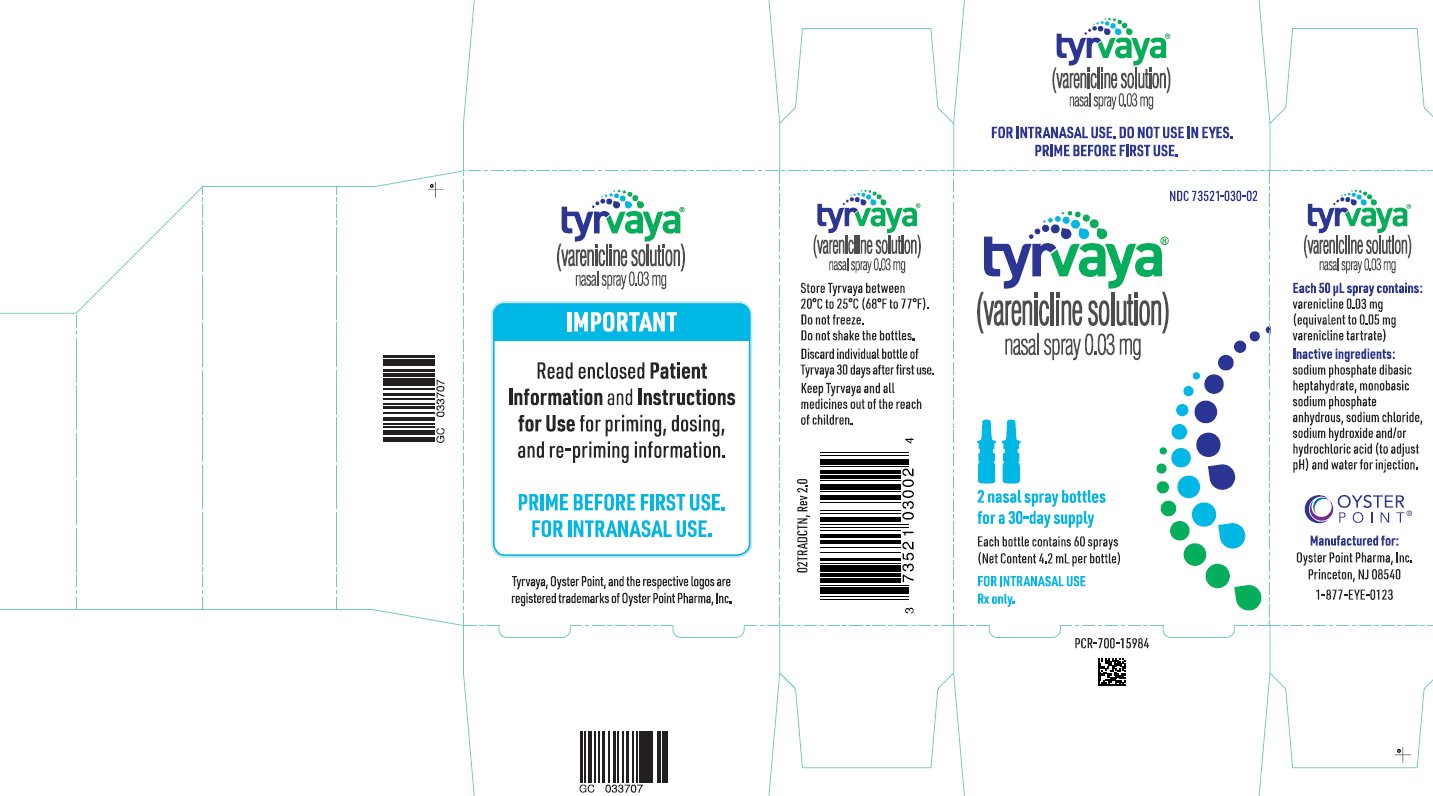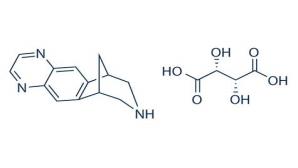 DRUG LABEL: Tyrvaya
NDC: 73521-030 | Form: SPRAY
Manufacturer: Oyster Point Pharma, Inc.
Category: prescription | Type: HUMAN PRESCRIPTION DRUG LABEL
Date: 20240212

ACTIVE INGREDIENTS: VARENICLINE TARTRATE 0.03 mg/0.05 mL
INACTIVE INGREDIENTS: SODIUM PHOSPHATE, DIBASIC, HEPTAHYDRATE; SODIUM PHOSPHATE, MONOBASIC, ANHYDROUS; SODIUM CHLORIDE; SODIUM HYDROXIDE; HYDROCHLORIC ACID; WATER

HIGHLIGHTS OF PRESCRIBING INFORMATION

These highlights do not include all the information needed to use TYRVAYA safely and effectively. See full prescribing information for TYRVAYA.
TYRVAYA® (varenicline solution) nasal spray
Initial U.S. Approval: 2006

1 INDICATIONS AND USAGE

TYRVAYA (varenicline solution) nasal spray is a cholinergic agonist indicated for the treatment of the signs and symptoms of dry eye disease. (1)

2 DOSAGE AND ADMINISTRATION

- One spray in each nostril twice daily (approximately 12 hours apart). (2.1)
- Prime with seven (7) actuations before initial use. Re-prime with 1 actuation if not used for more than five (5) days. (2.2)

3 DOSAGE FORMS AND STRENGTHS

Nasal spray delivering 0.03 mg of varenicline in each spray (0.05 mL). (3)

4 CONTRAINDICATIONS

None.

6 ADVERSE REACTIONS

The most common adverse reaction reported in 82% of patients was sneezing. Events that were reported in 5-16% of patients were cough, throat irritation, and instillation-site (nose) irritation. (6)

To report SUSPECTED ADVERSE REACTIONS, contact Oyster Point Pharma at 1-877-EYE-0123 or FDA at 1-800-FDA-1088 or www.fda.gov/medwatch.

FULL PRESCRIBING INFORMATION

1 INDICATIONS AND USAGE

TYRVAYA (varenicline solution) nasal spray is indicated for the treatment of the signs and symptoms of dry eye disease.

2 DOSAGE AND ADMINISTRATION

2.1 Dosing Information

Spray TYRVAYA once in each nostril twice daily (approximately 12 hours apart). If a dose is missed, resume regular dosing at the next scheduled dose time.

2.2 Priming Instructions

Priming: Prime TYRVAYA before initial use by pumping seven (7) actuations into the air away from the face. When TYRVAYA has not been used for more than 5 days, re-prime with 1 spray into the air. Do not shake.

3 DOSAGE FORMS AND STRENGTHS

Nasal spray delivering 0.03 mg of varenicline in each spray (0.05 mL).

4 CONTRAINDICATIONS

None

6 ADVERSE REACTIONS

6.1 Clinical Trials Experience

Because clinical trials are conducted under widely varying conditions, adverse reaction rates observed in the clinical trials of a drug cannot be directly compared to rates in the clinical trials of another drug and may not reflect the rates observed in practice.

In three clinical studies of dry eye disease conducted with varenicline solution nasal spray, 349 patients received at least 1 dose of TYRVAYA. The majority of patients had 31 days of treatment exposure, with a maximum exposure of 105 days.

The most common adverse reactions reported in 82% of TYRVAYA treated patients was sneezing. Other common adverse reactions that were reported in >5% of patients include cough (16%), throat irritation (13%), and instillation-site (nose) irritation (8%).

8 USE IN SPECIFIC POPULATIONS

8.1 Pregnancy

Risk Summary

There are no available data on TYRVAYA use in pregnant women to inform any drug associated risks. In animal reproduction studies, varenicline did not produce malformations at clinically relevant doses.

All pregnancies have a risk of birth defect, loss, or other adverse outcomes. In the US general population, the estimated background risk of major birth defects and miscarriage in clinically recognized pregnancies is 2% to 4% and 15% to 20%, respectively.

Data

Animal Data

Pregnant rats and rabbits received varenicline succinate during organogenesis at oral doses up to 15 and 30 mg/kg/day, respectively. While no fetal structural abnormalities occurred in either species, maternal toxicity, characterized by reduced body weight gain, and reduced fetal weights occurred in rabbits at the highest dose (4864 times the MRHD on a mg/m^2 basis).

In a pre- and postnatal development study, pregnant rats received up to 15 mg/kg/day of oral varenicline succinate from organogenesis through lactation. Maternal toxicity, characterized by a decrease in body weight gain, was observed at 15 mg/kg/day (1216 times the MRHD on a mg/m^2 basis). Decreased fertility and increased auditory startle response occurred in offspring at the highest maternal dose of 15 mg/kg/day.

8.2 Lactation

Risk Summary

There are no data on the presence of varenicline in human milk, the effects on the breastfed infant, or the effects on milk production. In animal studies varenicline was present in milk of lactating rats. However, due to species-specific differences in lactation physiology, animal data may not reliably predict drug levels in human milk.

The lack of clinical data during lactation precludes a clear determination of the risk of TYRVAYA to an infant during lactation; however, the developmental and health benefits of breastfeeding should be considered along with the mother’s clinical need for TYRVAYA and any potential adverse effects on the breastfed child from TYRVAYA.

8.4 Pediatric Use

Safety and efficacy of TYRVAYA in pediatric patients have not been established.

8.5 Geriatric Use

No overall differences in safety or effectiveness have been observed between elderly and younger adult patients.

11 DESCRIPTION

TYRVAYA nasal spray contains varenicline which is a partial nicotinic acetylcholine receptor agonist of α4β2, α4α6β2, α3β4, and α3α5β4 receptors and a full α7 receptor agonist.

Varenicline, as the tartrate salt, is a powder which is a white to off-white to slightly yellow solid whose chemical name is 7,8,9,10-tetrahydro-6,10-methano-6H-pyrazino[2,3-h][3]benzazepine, (2R,3R)-2,3-dihydroxybutanedioate (1:1). It is highly soluble in water. Varenicline tartrate has a molecular weight of 361.35 Daltons and a molecular formula of C13H13N3 ⋅ C4H6O6. The chemical structure is:

TYRVAYA (varenicline solution) nasal spray is formulated for intranasal use as a clear 0.6 mg/mL strength solution, at pH 6.4. After priming [see Dosage and Administration (2.2)], each actuation delivers a 0.05 mL spray containing 0.03 mg varenicline free base, equivalent to 0.05 mg of varenicline tartrate. The formulation also contains the following inactive ingredients: sodium phosphate dibasic heptahydrate, monobasic sodium phosphate anhydrous, sodium chloride, sodium hydroxide and/or hydrochloric acid (to adjust pH) and water for injection.

12 CLINICAL PHARMACOLOGY

12.1 Mechanism of Action

The efficacy of TYRVAYA in dry eye disease is believed to be the result of varenicline's activity at heteromeric sub-type(s) of the nicotinic acetylcholine (nACh) receptor where its binding produces agonist activity and activates the trigeminal parasympathetic pathway resulting in increased production of basal tear film as a treatment for dry eye disease. Varenicline binds with high affinity and selectivity at human α4β2, α4α6β2, α3β4, α3α5β4 and α7 neuronal nicotinic acetylcholine receptors. The exact mechanism of action is unknown at this time.

12.3 Pharmacokinetics

Absorption/Distribution

Following administration of 0.12 mg (0.06 mg per 50-µL spray in each nostril), a strength of varenicline that is higher than the labeled concentration, varenicline can be detected in plasma by 5 minutes, generally achieves peak concentration within 2 hours, with a mean Cmax of 0.34 ng/mL, and has an AUC0-inf of 7.46 h*ng/mL. The systemic exposure (AUC0-inf) following this intranasal dose was approximately 7.5% of the exposure observed following a 1 mg oral dose of varenicline.

Metabolism/Elimination

The mean ± SD elimination half-life of varenicline after intranasal administration is approximately 19 ± 10 hours. Varenicline undergoes minimal metabolism with 92% excreted as unchanged drug in the urine.

13 NONCLINICAL TOXICOLOGY

13.1 Carcinogenesis, Mutagenesis, Impairment of Fertility

Carcinogenesis

Lifetime carcinogenicity studies were performed in CD-1 mice and Sprague-Dawley rats. There was no evidence of a carcinogenic effect in mice administered varenicline by oral gavage for 2 years at doses up to 20 mg/kg/day (810 times the maximum recommended human dose [MRHD], on a mg/m^2 basis). Rats were administered varenicline (1, 5, and 15 mg/kg/day) by oral gavage for 2 years. In male rats (n = 65 per sex per dose group), incidences of hibernoma (tumor of the brown fat) were increased at the mid dose (1 tumor, 5 mg/kg/day, 405 times the MRHD on a mg/m^2 basis) and maximum dose (2 tumors, 15 mg/kg/day, 1216 times the MRHD on a mg/m^2 basis). The clinical relevance of this finding to humans has not been established. There was no evidence of carcinogenicity in female rats.

Mutagenesis

Varenicline was not genotoxic, with or without metabolic activation, in the following assays: Ames bacterial mutation assay; mammalian CHO/HGPRT assay; and tests for cytogenetic aberrations in vivo in rat bone marrow and in vitro in human lymphocytes.

Impairment of Fertility

There was no evidence of impairment of fertility in either male or female Sprague-Dawley rats administered varenicline succinate up to 15 mg/kg/day (1216 times the MRHD on a mg/m^2 basis). Maternal toxicity, characterized by a decrease in body weight gain, was observed at 15 mg/kg/day. A decrease in fertility was noted in the offspring of pregnant rats administered varenicline succinate at an oral dose of 15 mg/kg/day. The decrease in fertility in the offspring of treated female rats was not evident at an oral dose of 3 mg/kg/day (243 times the MRHD, on a mg/m^2 basis).

14 CLINICAL STUDIES

The efficacy of TYRVAYA for the treatment of dry eye disease was supported by two randomized, multi-center, double-masked, vehicle-controlled studies (ONSET-1 and ONSET-2). In the ONSET-1 study, 182 patients were randomized in a 1:1:1:1 ratio to receive one spray in each nostril twice daily of varenicline solution 0.006 mg (N=47), TYRVAYA 0.03 mg (N=48), varenicline solution 0.06 mg (N=44), or vehicle (N=43). In the ONSET-2 study, 758 patients were randomized in a 1:1:1 ratio to receive one spray in each nostril twice daily of TYRVAYA 0.03 mg (N=260), varenicline solution 0.06 mg (N=246), or vehicle (N=252).

The majority of patients were female (74%), the mean (standard deviation [SD]) age was 61 (12.5) years, the mean (SD) baseline anesthetized Schirmer’s score was 5.1 mm (2.9), and the mean (SD) baseline eye dryness score (EDS) was 59.3 (21.6). Use of artificial tears was allowed during the studies. Enrollment criteria included minimal signs [i.e., anesthetized Schirmer's test score (range, 0-10 mm) and corneal fluorescein staining (range, 2-14)] and was not limited by baseline EDS (range, 2-100).

Efficacy

Tear film production was measured by anesthetized Schirmer’s score assessed using a Schirmer’s strip (0-35 mm). The average baseline Schirmer’s score was 5.0 mm in the ONSET-1 study and 5.1 mm in the ONSET-2 study. Of the patients treated with TYRVAYA, 52% achieved ≥10 mm increase in Schirmer’s score from baseline in the ONSET-1 study and 47% achieved ≥10 mm increase in Schirmer’s score from baseline in the ONSET-2 study, compared to 14% and 28% of vehicle-treated patients in the ONSET-1 study and the ONSET-2 study, respectively at Day 28 (see Table 1). Of the patients treated with TYRVAYA, the mean change in Schirmer’s score was 11.7 mm and 11.3 mm as compared to 3.2 mm and 6.3 mm in the vehicle treated patients in the ONSET-1 study and ONSET-2 study, respectively at Day 28.

Table 1: Percent of Patients Achieving ≥10 mm Improvement from Baseline in Schirmer’s Score in 28-day Studies in Patients with Dry Eye Disease
 | ONSET-1 |  | ONSET-2
 | TYRVAYA N=48 | Vehicle N=43 | TYRVAYA N=260 | Vehicle N=252
≥ 10-mm increase in tear production (% of eyes) at Day 28 | 52% | 14% | 47% | 28%
Proportion Difference (95% CI) | 38% (21%, 56%) |  | 20% (11%, 28%)
p-value versus control | <0.01 |  | <0.01

Cochran-Mantel-Haenszel (CMH) test controlling for study site, baseline Schirmer’s test score (STS), and baseline EDS.
All randomized and treated patients were included in the analysis and missing data were imputed using last-available data.

16 HOW SUPPLIED/STORAGE AND HANDLING

16.1 How Supplied

TYRVAYA (varenicline solution) nasal spray is available in a carton containing two (2) nasal spray amber glass Type I bottles. Each bottle consists of a white nasal pump and blue dust cover, delivering 0.03 mg varenicline per spray (0.05 mL). Each bottle delivers one spray in each nostril twice daily for 15 days.

Two nasal spray bottles in each carton, containing 60 sprays per bottle, equivalent to 30-days’ supply with one spray in each nostril twice daily (NDC 73521-030-02).

16.2 Storage and Handling

- Store TYRVAYA nasal spray at 20°C to 25°C (68°F to 77°F). Do not freeze.
- Discard TYRVAYA nasal spray bottle 30 days after opening bottle.

17 PATIENT COUNSELING INFORMATION

- Advise the patient to read the FDA-approved patient labeling (Patient Information and Instructions for Use).
- Instruct patients that TYRVAYA works to increase tear production in the eye after being sprayed in the nose.
- Instruct patients to prime the bottle before using it for the first time by pumping seven (7) sprays into the air away from the face and to re-prime it by pumping 1 spray into the air away from the face if the bottle has not been used in more than five (5) days.
- Instruct patients to wipe the nasal applicator with a clean tissue after each use.
- Instruct patients to not shake or freeze the bottle.

Manufactured for: Oyster Point Pharma, Inc., a Viatris company, 202 Carnegie Center, Suite 106, Princeton, NJ 08540

Copyrights and Trademarks are property of their respective owners.

TYRVAYA® is a registered trademark of Oyster Point Pharma, Inc., a Viatris company.

TYRVAYA® and/or the use of TYRVAYA® in a method may be covered by one or more patents or patent applications, available at www.oysterpointrx.com/patent-notices.

©2023 Oyster Point Pharma, Inc., a Viatris Company. All Rights Reserved.

OYP:TYRVA:R1

Patient Package Insert

TYRVAYA® (Teer-vye-ah)

(varenicline solution)

nasal spray, for intranasal use

What is TYRVAYA?

TYRVAYA is a prescription nasal spray used to treat the signs and symptoms of dry eye disease.

Before you use TYRVAYA, tell your healthcare provider about all of your medical conditions, including if you:

- are pregnant or plan to become pregnant. It is not known if TYRVAYA will harm your unborn baby.
- are breastfeeding or plan to breastfeed. It is not known if TYRVAYA passes into your breast milk. You and your healthcare provider should decide if you will use TYRVAYA if you plan to breastfeed.

Tell your healthcare provider about all the medicines you take, including prescription and over-the-counter medicines, vitamins, and herbal supplements.

Know the medicines you take. Keep a list of them to show your healthcare provider and pharmacist when you get a new medicine.

How should I use TYRVAYA?

- See the Instructions for Use at the end of this Patient Information leaflet for information about the right way to use TYRVAYA.
- TYRVAYA increases tear production in the eye after being sprayed in the nose.
- Use TYRVAYA exactly as your healthcare provider tells you to use it.
- Do not shake the bottles.
- Spray TYRVAYA 1 time in each nostril, 2 times daily (about 12 hours apart).
- A 1-month supply of TYRVAYA consists of 2 nasal spray bottles. Finish 1 bottle before opening the second. TYRVAYA comes in glass bottles with a white nasal pump and blue dust cover.
- If you miss a dose of TYRVAYA, skip that dose and take your next dose at your regular scheduled time. Do not take an extra dose to make up for a missed dose.

What are the possible side effects of TYRVAYA?

The most common side effects of TYRVAYA include sneezing, cough, and throat and nose irritation.

These are not the only possible side effects of TYRVAYA. Call your doctor for medical advice about side effects.

You may report side effects to FDA at 1-800-FDA-1088.

How should I store TYRVAYA?

- Store TYRVAYA at room temperature between 68°F to 77°F (20°C to 25°C).
- Do not freeze.
- Throw away (discard) TYRVAYA nasal spray bottle 30 days after first use.

Keep TYRVAYA and all medicines out of the reach of children.

General information about the safe and effective use of TYRVAYA.

Medicines are sometimes prescribed for purposes other than those listed in a Patient Information leaflet. Do not use TYRVAYA for a condition for which it was not prescribed. Do not give TYRVAYA to other people, even if they have the same symptoms that you have. It may harm them. You can ask your pharmacist or healthcare provider for information about TYRVAYA that is written for health professionals.

What are the ingredients in TYRVAYA?

Active ingredient: varenicline tartrate

Inactive ingredients: sodium phosphate dibasic heptahydrate, monobasic sodium phosphate anhydrous, sodium chloride, sodium hydroxide and/or hydrochloric acid (to adjust pH) and water for injection.

TYRVAYA® is a registered trademark of Oyster Point Pharma, Inc., a Viatris Company.

TYRVAYA® and/or the use of TYRVAYA® in a method may be covered by one or more patents or patent applications, available at www.oysterpointrx.com/patent-notices.

Manufactured for: Oyster Point Pharma, Inc., 202 Carnegie Center, Suite 106, Princeton, NJ 08540

This Patient Information has been approved by the U.S. Food and Drug Administration

Revised: 2/2024

OYP:PL:TYRVA:R1

Instructions for Use

TYRVAYA® (Teer-vye-ah)
(varenicline solution)
nasal spray, for intranasal use

Read this Instructions for Use before you start using TYRVAYA and each time you get a refill. There may be new information. This information does not take the place of talking to your healthcare provider about your medical condition or your treatment.

Important information you need to know before using TYRVAYA:

Parts of your TYRVAYA nasal spray:

- TYRVAYA is for use in the nose.
- Do not shake the bottles.
- The TYRVAYA carton contains enough medicine for 30 days.
  - Each carton has 2 glass nasal spray bottles.
  - Each nasal spray bottle has enough medicine for 15 days of treatment.
  - Do not open the second nasal spray bottle until you have used the entire first bottle.

Steps for priming TYRVAYA before first Use

Step 1. Remove the cap and the clip.
Do not throw away the cap or the clip. The cap and the clip will be placed back on to the nasal applicator after each use.

Step 2. Hold the nasal spray bottle upright and away from your face. Place 1 finger on each side of the base of the nasal applicator and place your thumb underneath the bottle.

Step 3. Prime the nasal spray bottle by fully pressing and releasing the nasal applicator 7 times with your thumb and fingers. You may feel some resistance but be sure to press all the way down. You may not see a spray released each time you press and release the nasal applicator. You should see a spray by the 7th time you press and release. Spray away from yourself and others.
TYRVAYA is now primed for use.

- Reprime: If you do not use TYRVAYA for more than 5 days, you will need to reprime the nasal spray bottle with 1 spray before you start using it. To reprime, hold the nasal spray bottle upright and away from your face and fully press and release the nasal spray applicator 1 time.
- Avoid priming the nasal spray bottle more than needed: Priming the nasal spray bottle more than needed will reduce the amount of medicine in the nasal spray bottle.

Steps for using TYRVAYA nasal spray after priming

Step 1. Blow your nose to clear your nostrils, if needed.

Step 2. Remove the cap and clip.
Do not throw away the cap or the clip. The cap and the clip will be placed back on to the nasal applicator after each use.

Step 3. Hold the nasal spray bottle upright. Place 1 finger on each side of the base of the nasal applicator and your thumb underneath the bottle.

Step 4. Tilt your head back slightly without lying down.

Step 5. Insert the nasal applicator into the left or right nostril. Tilt the nasal applicator and point the tip of the nasal applicator towards the top of the ear on the same side as your nostril.
Do not press the tip of the nasal applicator against the wall of the inside of your nose. Leave a space between the tip of the nasal applicator and the wall of the inside of your nose.

Step 6. Place your tongue to the roof of your mouth and breathe gently while fully pressing and releasing the nasal applicator 1-time to release a spray into your nostril.
Repeat Steps 5 and 6 to deliver a second spray in the other nostril.

Step 7. Wipe the nasal applicator with a clean tissue.

Step 8. Replace the clip and the cap.
Repeat Steps 1 to 8 each time you use TYRVAYA.

This Instructions for Use has been approved by the U.S. Food and Drug Administration.

TYRVAYA® is a registered trademark of Oyster Point Pharma, Inc., a Viatris company.

TYRVAYA® and/or the use of TYRVAYA® in a method may be covered by one or more patents or patent applications, available at www.oysterpointrx.com/patent-notices.

Manufactured for: Oyster Point Pharma, Inc., 202 Carnegie Center, Suite 106, Princeton, NJ 08540

©2023 Oyster Point Pharma, Inc.

Revised: 2/2024

OYP:IFU:TYRVA:R1

PRINCIPAL DISPLAY PANEL - NASAL SPRAY 0.03 mg

NDC 73521-030-02

tyrvaya®
(varenicline solution)
nasal spray 0.03 mg

2 nasal spray bottles
for a 30-day supply

Each bottle contains 60 sprays
(Net Content 4.2 mL per bottle)

FOR INTRANASAL USE

Rx only.

Each 50 μL spray contains:
varenicline 0.03 mg
(equivalent to 0.05 mg
varenicline tartrate)

Inactive ingredients:
sodium phosphate dibasic
heptahydrate, monobasic
sodium phosphate
anhydrous, sodium chloride,
sodium hydroxide and/or
hydrochloric acid (to adjust
pH) and water for injection.

Manufactured for:
Oyster Point Pharma, Inc.
Princeton, NJ 08540

1-877-EYE-0123

Store Tyrvaya between
20°C to 25°C (68°F to 77°F).

Do not freeze.

Do not shake the bottles.

Discard individual bottle of
Tyrvaya 30 days after first use.

Keep Tyrvaya and all
medicines out of the reach
of children.

02TRADCTN, Rev 2.0

IMPORTANT

Read enclosed Patient

Information and Instructions

for Use for priming, dosing,

and re-priming information.

PRIME BEFORE FIRST USE.

FOR INTRANASAL USE.

Tyrvaya, Oyster Point, and the respective logos
are registered trademarks of Oyster Point Pharma, Inc.